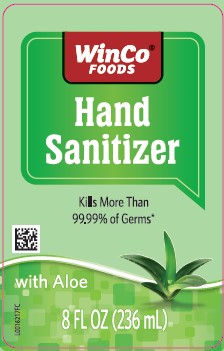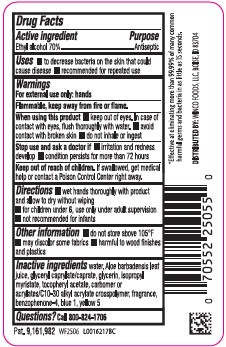 DRUG LABEL: Advanced Hand Sanitizer
NDC: 67091-439 | Form: GEL
Manufacturer: Winco Foods
Category: otc | Type: HUMAN OTC DRUG LABEL
Date: 20260212

ACTIVE INGREDIENTS: ALCOHOL 700 mg/1 mL
INACTIVE INGREDIENTS: WATER; ALOE VERA LEAF; GLYCERYL CAPRYLATE/CAPRATE; GLYCERIN; ISOPROPYL MYRISTATE; .ALPHA.-TOCOPHEROL ACETATE; CARBOMER INTERPOLYMER TYPE A (ALLYL SUCROSE CROSSLINKED); SULISOBENZONE; FD&C BLUE NO. 1; FD&C YELLOW NO. 5

Winco 439.001/439AC
Advanced Hand Sanitizer with Aloe

active ingredient

Ethyl Alcohol 70%

Purpose

Antiseptic

Uses

- to decrease bacteria on the skin that could cause disease
- recommended for repeated use

Warnings

For external use only: hands

Flammable, keep away from heat and flame.

When using this product

- keep out of eyes. In case of contact with eyes, flush thoroughly with water.
- avoid contact with broken skin
- do not inhale or ingest

Stop use and ask a doctor if

- irritation and redness develop
- condition persists for more than 72 hours

Keep out of reach of children.

If swallowed, get medical help or contact a Poison Control Center right away.

Directions

- wet hands thoroughly with product and allow to dry without wiping
- for children under 6, use only under adult supervision
- not recommended for infants

Inactive ingredients

water, aloe barbadensis leaf juice, glyceryl caprylate/caprate, glycerin, isopropyl myristate, tocopheryl acetate, acrylates/C10-30 alkyl acrylate crosspolymer, fragrance, benzophenone-4, blue 1, yellow 5

Questions?

Call 800-824-1706

ADVERSE REACTION

*Effective at eliminating more than 99.99% of many common harmful germs and bacteria in as little as 15 seconds.

DISTRIBUTED BY: WINCO FOODS, LLC, BOISE, ID 83704

Pat. 9, 161, 982

principal display panel

WinCo® FOODS

HAND SANITIZER

Kills More Than 99.99% of Germs*

with Aloe

8 FL OZ (236 mL)